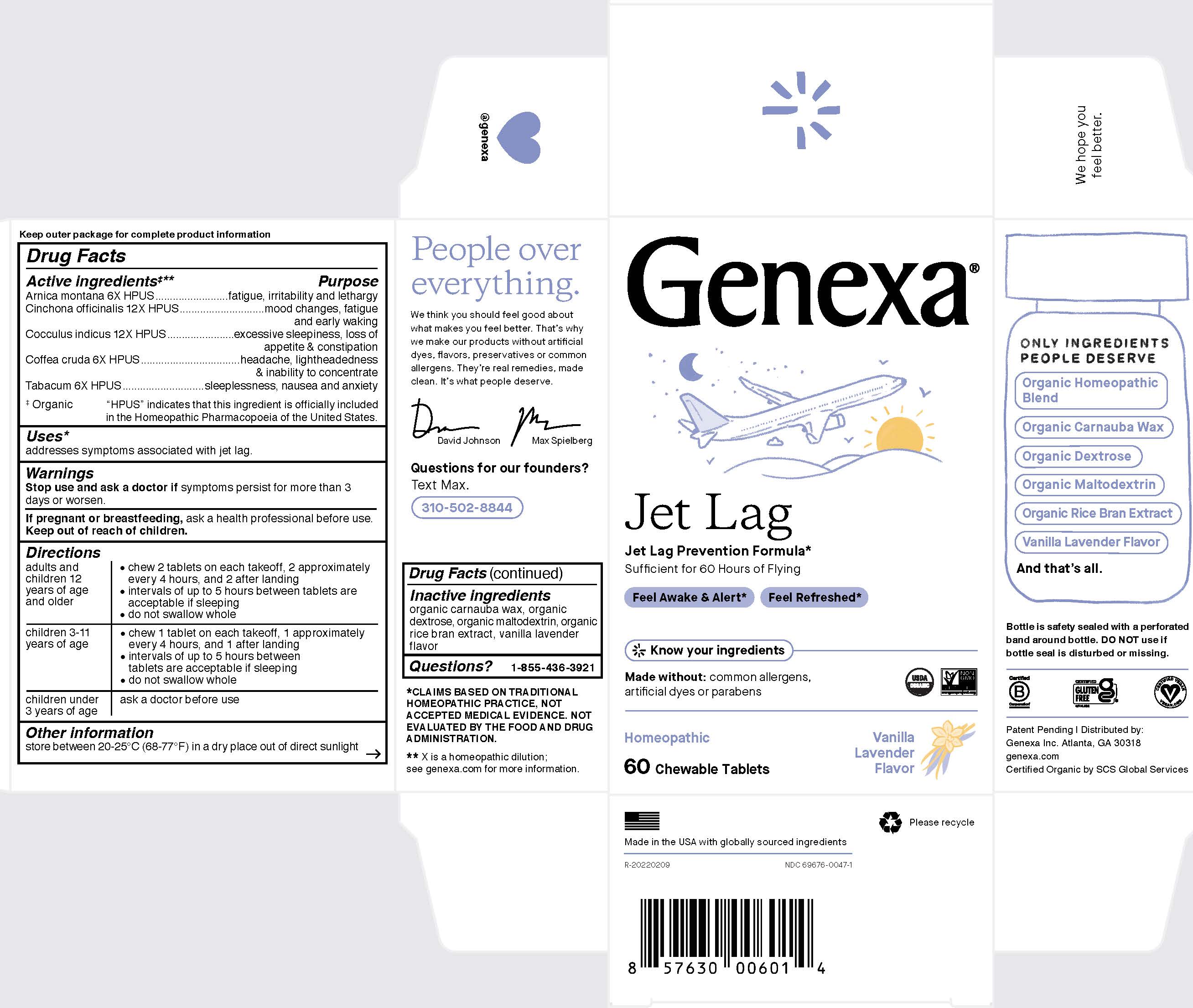 DRUG LABEL: Genexa Jet Lag
NDC: 69676-0047 | Form: TABLET, CHEWABLE
Manufacturer: Genexa Inc.
Category: homeopathic | Type: HUMAN OTC DRUG LABEL
Date: 20250226

ACTIVE INGREDIENTS: ARABICA COFFEE BEAN 6 [hp_X]/1 1; ANAMIRTA COCCULUS SEED 12 [hp_X]/1 1; TOBACCO LEAF 6 [hp_X]/1 1; CINCHONA OFFICINALIS BARK 12 [hp_X]/1 1; ARNICA MONTANA 6 [hp_X]/1 1
INACTIVE INGREDIENTS: MALTODEXTRIN; RICE BRAN; CARNAUBA WAX; DEXTROSE

JET LAG ADULT

Keep outer package for complete product information

Drug Facts

Active ingredients‡**

Arnica montana 6X HPUS

Cinchona officinalis 12X HPUS

Cocculus indicus 12X HPUS

Coffea cruda 6X HPUS

Tabacum 6X HPUS

‡ Organic

"HPUS" indicates that this ingredient is officially included in the Homeopathic Pharmacopoeia of the United States.

Purpose

fatigue, irritability and lethargy

mood changes, fatigue and early waking

excessive sleepiness, loss of appetite & constipation

headache, lightheadedness & inability to concentrate

sleeplessness, nausea and anxiety

Uses*

addresses symptoms associated with jet lag.

Warnings

Stop use and ask a doctor if symptoms persist for more than 3 days or worsen.

PREGNANCY OR BREAST FEEDING

If pregnant or breastfeeding, ask a health professional before use.

Keep out of reach of children.

Directions

adults and children 12 years of age and older | - chew 2 tablets on each takeoff, 2 approximately every 4 hours, and 2 after landing - intervals of up to 5 hours between tablets are acceptable if sleeping - do not swallow whole.
children 3-11 years of age | - chew 1 tablet on each takeoff, 1 approximately every 4 hours, and 1 after landing - intervals of up to 5 hours between tablets are acceptable if sleeping - do not swallow whole
children under 3 years of age | ask a doctor before use.

Other information

store between 20-25°C (68-77°F) in a dry place out of direct sunlight

Inactive ingredients

organic carnauba wax, organic dextrose, organic maltodextrin, organic rice bran extract, vanilla lavender flavor

Questions?

1-855-436-3921

* CLAIMS BASED ON TRADITIONAL HOMEOPATHIC PRACTICE, NOT ACCEPTED MEDICAL EVIDENCE. NOT EVALUATED BY THE FOOD AND DRUG ADMINISTRATION.
** X is a homeopathic dilution: see www.genexa.com for more information.

Bottle is safety sealed with a perforated band around bottle. DO NOT use if bottle seal is disturbed or missing.

Patent Pending | Distributed by:

Genexa Inc. Atlanta, GA 30318

genexa.com

Certified Organic by SCS Global Services

Made in the USA with globally sourced ingredients

R-20220209

NDC 69676-0047-1

PACKAGE LABEL

Genexa®

Jet Lag

Jet Lag Prevention Formula*

Sufficient for 60 Hours of Flying

Feel Awake & Alert*

Feel Refreshed*

Know your ingredients

Made without: common allergens, artifical dyes or parabens

Homeopathic

60 Chewable Tablets

Vanilla Lavender Flavor